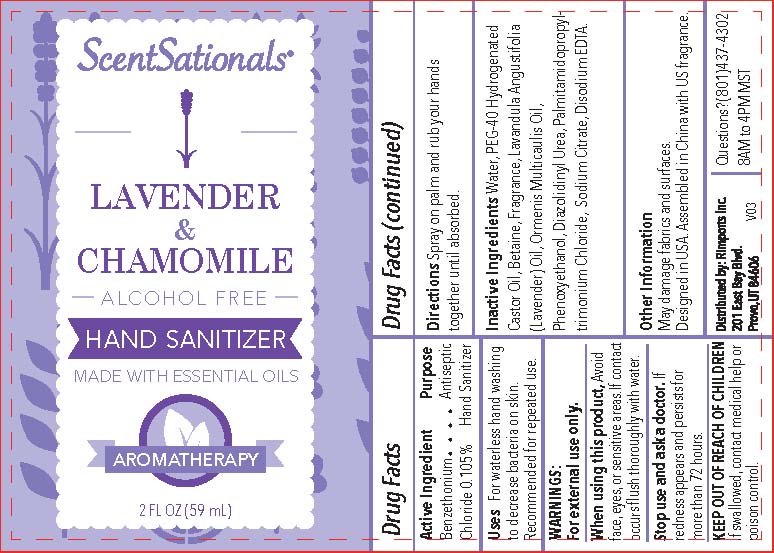 DRUG LABEL: Hand Sanitizer
NDC: 72131-005 | Form: GEL
Manufacturer: RIMPORTS INC.
Category: otc | Type: HUMAN OTC DRUG LABEL
Date: 20180315

ACTIVE INGREDIENTS: BENZETHONIUM CHLORIDE 0.105 g/100 mL
INACTIVE INGREDIENTS: DIAZOLIDINYL UREA; BETAINE; LAVANDULA ANGUSTIFOLIA FLOWER; CHAMOMILE FLOWER OIL; WATER; PALMITAMIDOPROPYLTRIMONIUM CHLORIDE; SODIUM CITRATE; EDETATE DISODIUM ANHYDROUS; PHENOXYETHANOL; POLYOXYL 40 HYDROGENATED CASTOR OIL

Active Ingredient:
Benzethonium Chloride 0.105%

Purpose

Antiseptic

Stop use and ask a doctor if redness appears and persists for more than 72 hours.

KEEP OUT OF REACH OF CHILDREN. If swallowed, contact medical help or poison control.

DOSAGE AND ADMINISTRATION

Directions Spray on palm and rub your hands together until absorbed.

Inactive Ingredients

Water, PEG-40 Hydrogenated Castor Oil, Betaine, Fragrance, Citrus Aurantium Dulcis (Orange) Peel Oil, Zingiber Offincinale (Ginger) Root Oil,, Phenoxyethanol, Diazolidinyl Urea, Palmitamidopropyltrimonium Chloride, Sodium Citrate, Disodium EDTA.

Other Information

May damage fabrics and surfaces.

Uses

For waterless hand washing to decrease bacteria on skin. Recommended for repeated use.

WARNINGS:

For external use only.

When using this product, Avoid face, eyes or sensitive areas. If contact occurs flush thoroughly with water.